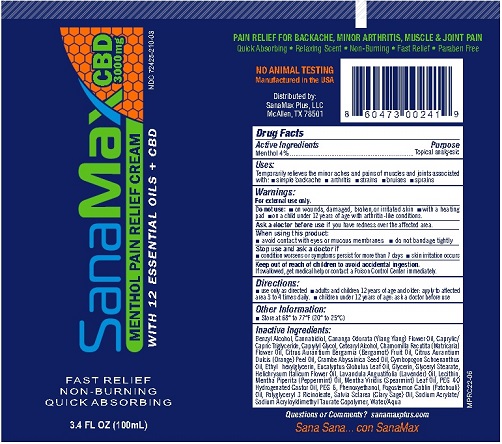 DRUG LABEL: SanaMax Menthol Pain Relief Cream
NDC: 72425-210 | Form: CREAM
Manufacturer: SanaMax Plus LLC
Category: otc | Type: HUMAN OTC DRUG LABEL
Date: 20241230

ACTIVE INGREDIENTS: MENTHOL 4.0 g/100 mL
INACTIVE INGREDIENTS: BENZYL ALCOHOL; CANNABIDIOL; YLANG-YLANG OIL; MEDIUM-CHAIN TRIGLYCERIDES; CAPRYLYL GLYCOL; CETOSTEARYL ALCOHOL; CHAMOMILE FLOWER OIL; BERGAMOT OIL; ORANGE OIL, COLD PRESSED; CRAMBE HISPANICA SUBSP. ABYSSINICA SEED OIL; CYMBOPOGON SCHOENANTHUS OIL; ETHYLHEXYLGLYCERIN; EUCALYPTUS OIL; GLYCERIN; GLYCERYL STEARATE CITRATE; HELICHRYSUM ITALICUM FLOWER OIL; LAVENDER OIL; LECITHIN, SUNFLOWER; PEPPERMINT OIL; SPEARMINT OIL; POLYOXYL 40 HYDROGENATED CASTOR OIL; POLYETHYLENE GLYCOL 300; PHENOXYETHANOL; POGOSTEMON CABLIN LEAF OIL; POLYGLYCERYL-3 RICINOLEATE; CLARY SAGE OIL; SODIUM ACRYLATE/SODIUM ACRYLOYLDIMETHYLTAURATE COPOLYMER (4000000 MW); WATER

SanaMax Menthol Pain Relief Cream

Drug Facts

Active Ingredients Menthol 4%

Purpose Topical analgesic

INDICATIONS AND USAGE

Uses: temporarily relieves the minor aches and pains of muscles and
joints associated with: ■ simple backache ■ arthritis ■ strains ■ bruises ■ sprains

Warnings
For external use only.

Do not use: ■ on wounds, damaged, broken, or irritated skin

■ with a heating pad ■ on a child under 12 years of age with

arthritis-like conditions.

Ask a doctor before use if you have redness over the affected area.

When using this product ■ avoid contact with eyes or mucous membrane

■ do not bandage tightly

Stop use and ask a doctor if
■ condition worsens or symptoms persist for more than 7 days
■ skin irritation occurs

Keep out of reach of children to avoid accidental ingestion.

If swallowed, get medical help or contact a Poison Control Center immediately.

Directions
■ use only as directed ■ adults and children 12 years of age and
older: apply to affected area 3 to 4 times daily
■ children under 12 years of age: ask a doctor before use

Other information:

■ Store at 68° to 77°F (20° to 25°C)

Inactive Ingredients:
Benzyl Alcohol, Cannabidiol, Cananga Odorata (Ylang Ylang) Flower Oil, Caprylic/
Capric Triglyceride, Caprylyl Glycol, Cetearyl Alcohol, Chamomilla Recutita (Matricaria)
Flower Oil, Citrus Aurantium Bergamia (Bergamot) Fruit Oil, Citrus Aurantium
Dulcis (Orange) Peel Oil, Crambe Abyssinica Seed Oil, Cymbopogon Schoenanthus
Oil, Ethyl- hexylglycerin, Eucalyptus Globulus Leaf Oil, Glycerin, Glyceryl Stearate,
Helichrysum Italicum Flower Oil, Lavandula Angustifolia (Lavender) Oil, Lecithin,
Mentha Piperita (Peppermint) Oil, Mentha Viridis (Spearmint) Leaf Oil, PEG-40
Hydrogenated Castor Oil, PEG-6, Phenoxyethanol, Pogostemon Cablin (Patchouli)
Oil, Polyglyceryl-3 Ricinoleate, Salvia Sclarea (Clary Sage) Oil, Sodium Acrylate/
Sodium Acryloyldimethyl Taurate Copolymer, Water/Aqua

Labeling

SanaMax

MENTHOL PAIN RELIEF CREAM
CBD 300mg

3.4 FL OZ (100mL)

Distributed by:
SanaMax Plus, LLC
McAllen, TX 78501

Questions or Comments? sanamaxplus.com

res